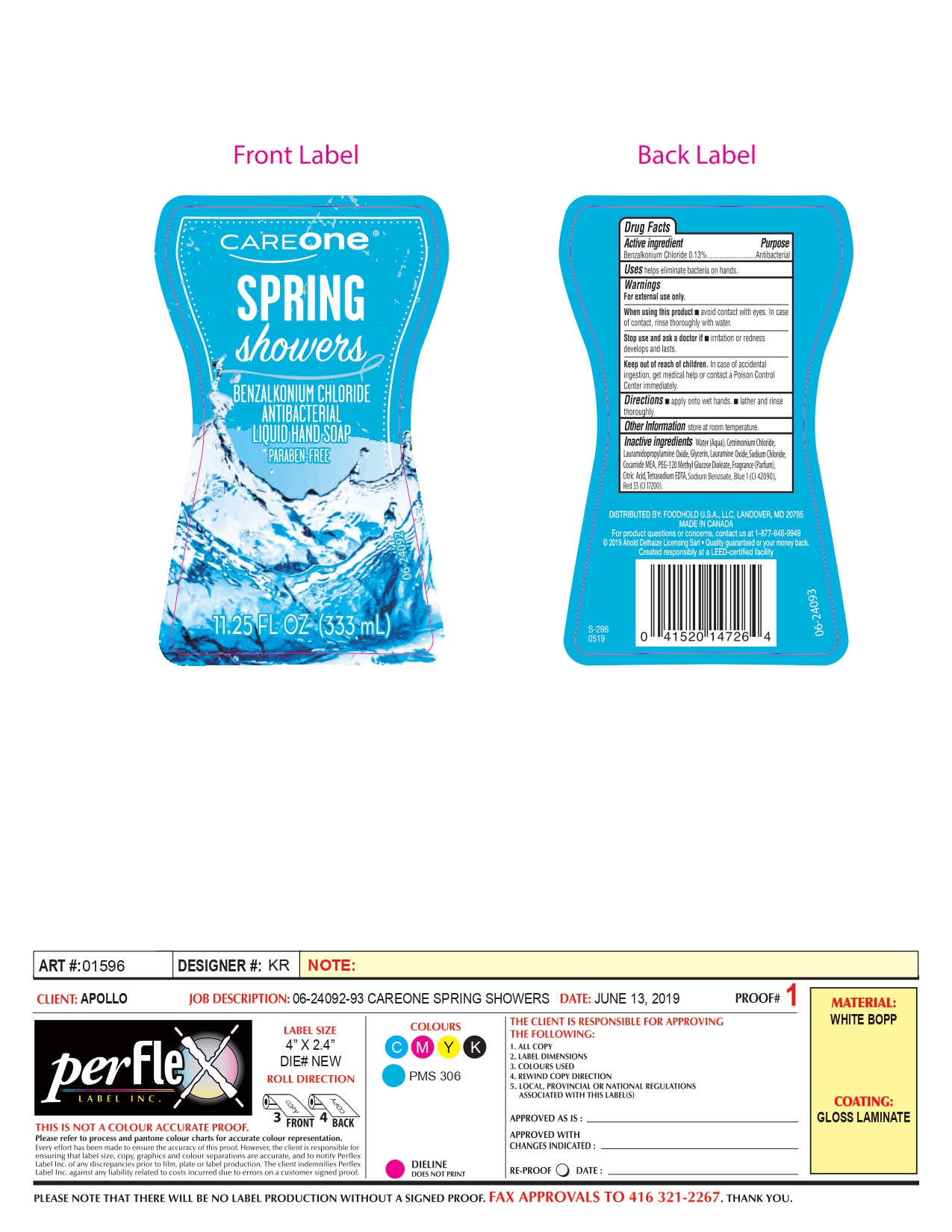 DRUG LABEL: Careone Spring Shower
NDC: 72476-006 | Form: SOAP
Manufacturer: Retail Business Services, LLC
Category: otc | Type: HUMAN OTC DRUG LABEL
Date: 20210914

ACTIVE INGREDIENTS: BENZALKONIUM CHLORIDE 130 mg/100 mL
INACTIVE INGREDIENTS: LAURAMINE OXIDE; COCO MONOETHANOLAMIDE; LAURAMIDOPROPYLAMINE OXIDE; SODIUM CHLORIDE; SODIUM BENZOATE; FD&C BLUE NO. 1; WATER; GLYCERIN; CETRIMONIUM CHLORIDE; PEG-120 METHYL GLUCOSE DIOLEATE; FRAGRANCE CLEAN ORC0600327; CITRIC ACID MONOHYDRATE; EDETATE SODIUM; D&C RED NO. 33

Drug Facts

Active Ingredient.

Benzalkonium Chloride (0.13%)

Purpose

Antibacterial

Uses

Helps eliminate bacteria on hands.

Warnings

For external use only

When using this product

Avoid contact with eyes. In case of contact, rinse thoroughly with water.

Stop use and ask a doctor.

If irritation or redness develops and lasts

Keep out of reach of children.

In case of accidental ingestion, get medical help or contact Poison Control Center immediately.

Directions

- apply onto wet hands
- Lather and rinse thoroughly

Other Information

Store at Room Temperature

Inactive Ingredients

Water (Aqua), Cetrimonium Chloride, Lauramidopropylamine Oxide, Glycerin, Lauramine Oxide, Sodium Chloride, Cocamide MEA, PEG-120 Methyl Glucose Dioleate, Fragrance (Parfum), Citric Acid, Tetrasodium EDTA, Sodium Benzoate, Blue 1 (Cl 42090), Red 33 (Cl 17200).